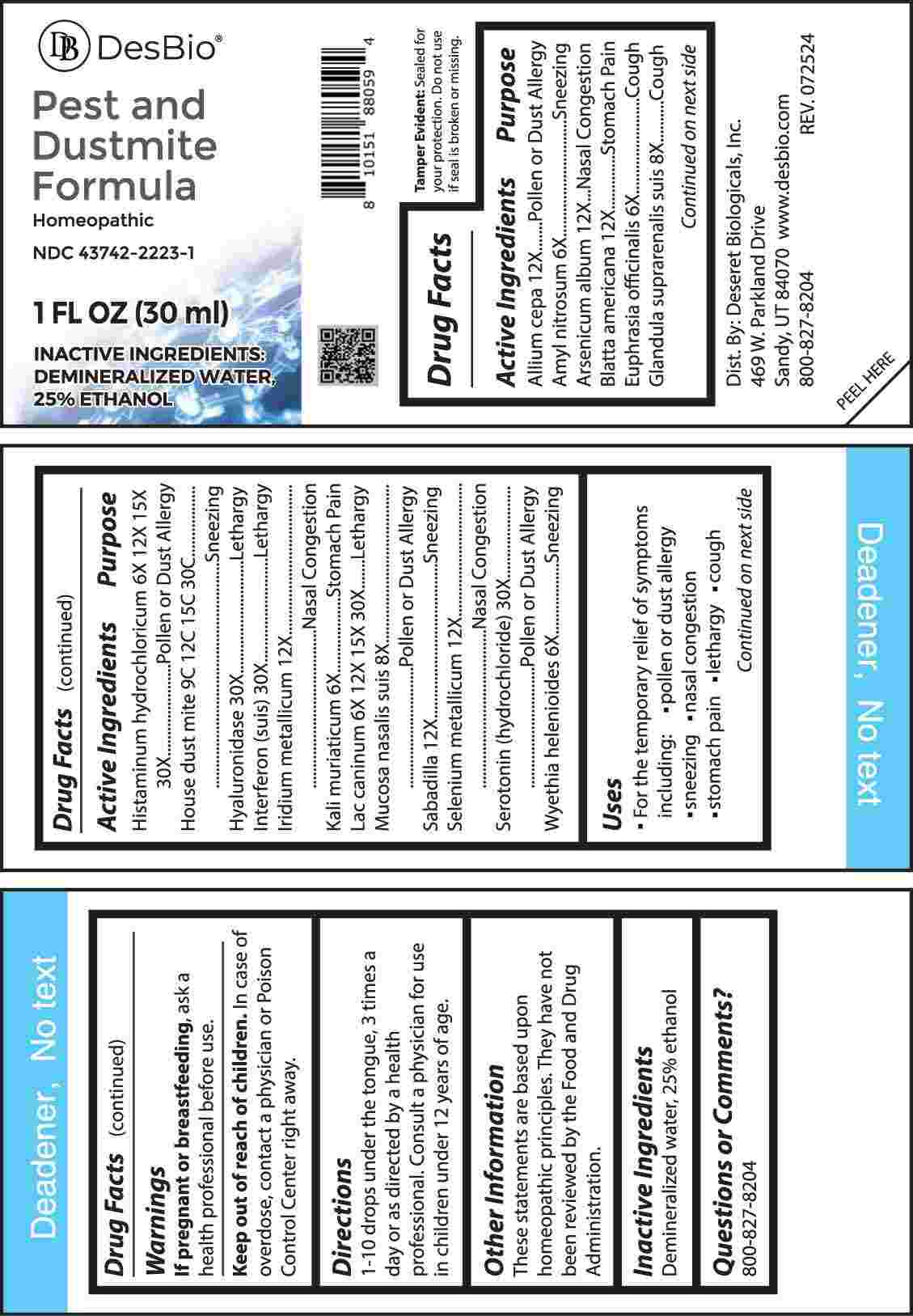 DRUG LABEL: Pest and Dustmite Formula
NDC: 43742-2223 | Form: LIQUID
Manufacturer: Deseret Biologicals, Inc.
Category: homeopathic | Type: HUMAN OTC DRUG LABEL
Date: 20241213

ACTIVE INGREDIENTS: ONION 12 [hp_X]/1 mL; AMYL NITRITE 6 [hp_X]/1 mL; ARSENIC TRIOXIDE 12 [hp_X]/1 mL; PERIPLANETA AMERICANA 12 [hp_X]/1 mL; EUPHRASIA STRICTA 6 [hp_X]/1 mL; SUS SCROFA ADRENAL GLAND 8 [hp_X]/1 mL; HISTAMINE DIHYDROCHLORIDE 6 [hp_X]/1 mL; DERMATOPHAGOIDES PTERONYSSINUS 9 [hp_C]/1 mL; HYALURONIDASE (BOVINE) 30 [hp_X]/1 mL; INTERFERON .GAMMA. PORCINE RECOMBINANT 30 [hp_X]/1 mL; IRIDIUM 12 [hp_X]/1 mL; POTASSIUM CHLORIDE 6 [hp_X]/1 mL; CANIS LUPUS FAMILIARIS MILK 6 [hp_X]/1 mL; SUS SCROFA NASAL MUCOSA 8 [hp_X]/1 mL; SCHOENOCAULON OFFICINALE SEED 12 [hp_X]/1 mL; SELENIUM 12 [hp_X]/1 mL; SEROTONIN HYDROCHLORIDE 30 [hp_X]/1 mL; WYETHIA HELENIOIDES ROOT 6 [hp_X]/1 mL
INACTIVE INGREDIENTS: WATER; ALCOHOL

DRUG FACTS:

ACTIVE INGREDIENTS:

Allium Cepa 12X, Amyl Nitrosum 6X, Arsenicum Album 12X, Blatta Americana 12X, Euphrasia Officinalis 6X, Glandula Suprarenalis Suis 8X, Histaminum Hydrochloricum 6X, 12X, 15X, 30X, House Dust Mite 9C, 12C, 15C, 30C, Hyaluronidase 30X, Interferon (Suis) 30X, Iridium Metallicum 12X, Kali Muriaticum 6X, Lac Caninum 6X, 12X, 15X, 30X, Mucosa Nasalis Suis 8X, Sabadilla 12X, Selenium Metallicum 12X, Serotonin (Hydrochloride) 30X, Wyethia Helenoides 6X.

PURPOSE:

Allium Cepa – Pollen or Dust Allergy, Amyl Nitrosum - Sneezing, Arsenicum Album – Nasal Congestion, Blatta Americana – Stomach Pain, Euphrasia Officinalis - Cough, Glandula Suprarenalis Suis - Cough, Histaminum Hydrochloricum – Pollen or Sust Allergy, House Dust Mite - Sneezing, Hyaluronidase - Lethargy, Interferon (Suis) - Lethargy, Iridium Metallicum – Nasal Congestion, Kali Muriaticum – Stomach Pain, Lac Caninum - Lethargy, Mucosa Nasalis Suis – Pollen or Dust Allergy, Sabadilla - Sneezing, Selenium Metallicum – Nasal Congestion, Serotonin (Hydrochloride) – Pollen or Dust Allergy, Wyethia Helenoides - Sneezing

USES:

• For the temporary relief of symptoms including:

• pollen or dust allergy • sneezing • nasal congestion • stomach pain • lethargy • cough

These statements are based upon homeopathic principles. They have not been reviewed by the Food and Drug Administration.

WARNINGS:

If pregnant or breast-feeding, ask a health professional before use.

Keep out of reach of children. In case of overdose, contact a physician or Poison Control Center right away.

Tamper Evident: Sealed for your protection. Do not use if seal is broken or missing.

KEEP OUT OF REACH OF CHILDREN:

In case of overdose, contact a physician or Poison Control Center right away.

DIRECTIONS:

1-10 drops under the tongue, 3 times a day or as directed by a health professional. Consult a physician for use in children under 12 years of age.

INACTIVE INGREDIENTS:

Demineralized Water, 25% Ethanol

QUESTIONS:

Dist. By: Deseret Biologicals, Inc.

469 W. Parkland Drive

Sandy, UT 84070

www.desbio.com

800-827-8204

PACKAGE LABEL DISPLAY:

DesBio

Pest and Dustmite Formula

Homeopathic

NDC 43742-2223-1

1 FL OZ (30 ml)